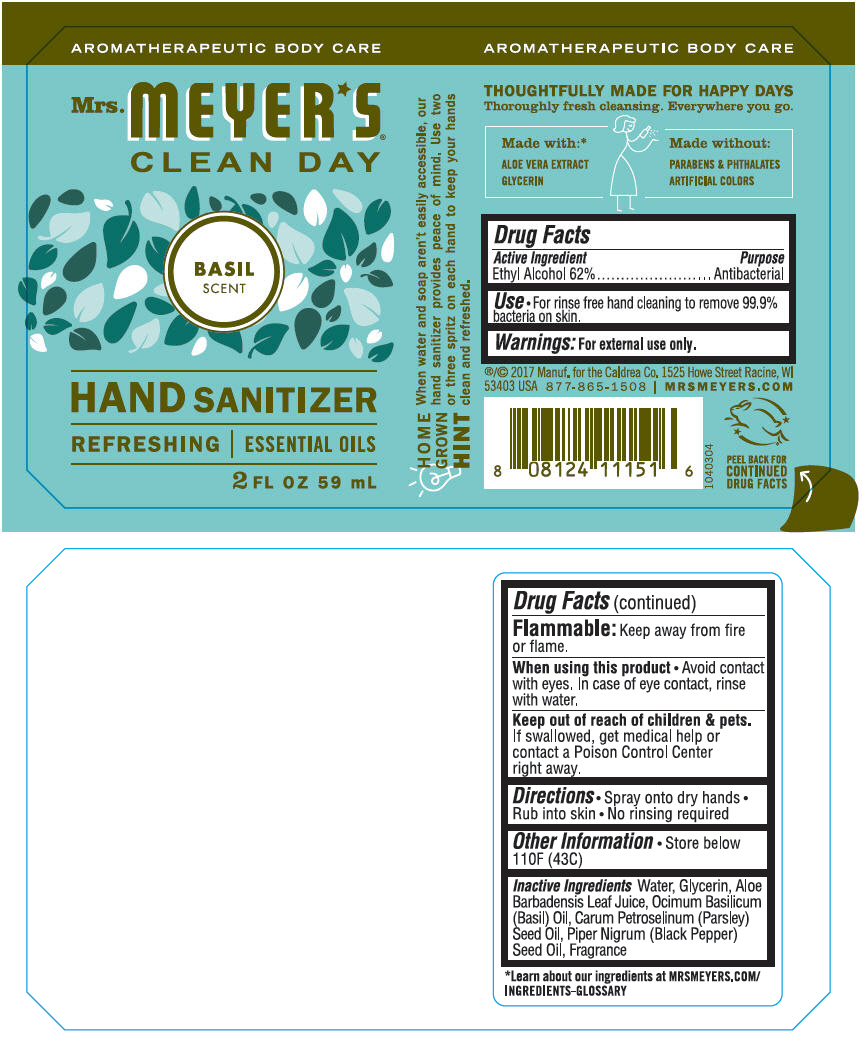 DRUG LABEL: Mrs. Meyers Clean Day Hand Sanitizer Basil Scent
NDC: 71763-101 | Form: SOLUTION
Manufacturer: The Caldrea Company
Category: otc | Type: HUMAN OTC DRUG LABEL
Date: 20251204

ACTIVE INGREDIENTS: ALCOHOL 0.62 mL/1 mL
INACTIVE INGREDIENTS: WATER; GLYCERIN; ALOE VERA LEAF; BASIL OIL; PARSLEY SEED OIL; WHITE PEPPER OIL

Mrs. Meyer's® Clean Day Hand Sanitizer Basil Scent

Drug Facts

Active Ingredient

Ethyl Alcohol 62%

Purpose

Antibacterial

Use

- For rinse free hand cleaning to remove 99.9% bacteria on skin.

Warnings

For external use only.

Flammable

Keep away from fire or flame.

When using this product

- Avoid contact with eyes. In case of eye contact, rinse with water.

Keep out of reach of children & pets. If swallowed, get medical help or contact a Poison Control Center right away.

Directions

- Spray onto dry hands
- Rub into skin
- No rinsing required

Other Information

- Store below 110F (43C)

Inactive Ingredients

Water, Glycerin, Aloe Barbadensis Leaf Juice, Ocimum Basilicum (Basil) Oil, Carum Petroselinum (Parsley) Seed Oil, Piper Nigrum (Black Pepper) Seed Oil, Fragrance

PRINCIPAL DISPLAY PANEL - 59 mL Bottle Label

AROMATHERAPEUTIC BODY CARE

Mrs. MEYER⋆S®
CLEAN DAY

BASIL
SCENT

HAND SANITIZER

REFRESHING | ESSENTIAL OILS

2 FL OZ 59 mL